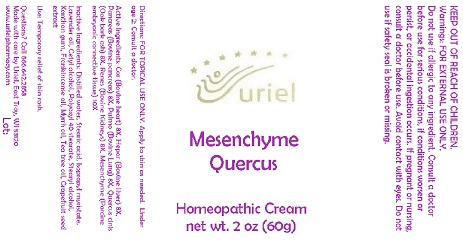 DRUG LABEL: Mesenchyme Quercus
NDC: 48951-7047 | Form: CREAM
Manufacturer: Uriel Pharmacy Inc.
Category: homeopathic | Type: HUMAN OTC DRUG LABEL
Date: 20170825

ACTIVE INGREDIENTS: BEEF HEART 8 [hp_X]/1 g; MAMMAL LIVER 8 [hp_X]/1 g; SUS SCROFA PANCREAS 8 [hp_X]/1 g; SUS SCROFA LUNG 8 [hp_X]/1 g; QUERCUS ROBUR WHOLE 8 [hp_X]/1 g; PORK KIDNEY 8 [hp_X]/1 g; BOS TAURUS CARTILAGE 10 [hp_X]/1 g
INACTIVE INGREDIENTS: WATER; STEARIC ACID; ISOPROPYL MYRISTATE; LAVENDER OIL; CETYL ALCOHOL; POLYOXYL 40 STEARATE; STEARYL ALCOHOL; XANTHAN GUM; POTASSIUM SORBATE; FRANKINCENSE OIL; MYRRH OIL; CITRUS PARADISI SEED

Mesenchyme Quercus

INDICATIONS AND USAGE

Directions: FOR TOPICAL USE ONLY.

DOSAGE AND ADMINISTRATION

Apply to skin as needed. Under age 2: Consult a doctor.

ACTIVE INGREDIENT

Active Ingredients: Cor (Bovine heart) 8X, Hepar (Bovine liver) 8X, Pancreas (Bovine pancreas) 8X, Pulmo (Bovine Lung) 8X, Quercus cinis (Oak bark ash) 8X, Renes (Bovine Kidneys) 8X, Mesenchyme (Porcine embryonic connective tissue) 10X

INACTIVE INGREDIENT

Inactive Ingredients: Distilled water, Stearic acid, Isopropyl myristate, Lavender oil, Cetyl alcohol, Polyoxyl 40 stearate, Stearyl alcohol, Xanthan gum, Potassium sorbate, Frankincense oil, Myrrh oil, Grapefruit seed extract

PURPOSE

Use: Temporary relief of skin rash.

KEEP OUT OF REACH OF CHILDREN.

WARNINGS

Warnings: FOR EXTERNAL USE ONLY. Do not use if allergic to any ingredient. Consult a doctor before use for serious conditions, if conditions worsen or persist, or accidental ingestion occurs. If pregnant or nursing, consult a doctor before use. Avoid contact with eyes. Do not use if safety seal is broken or missing.

QUESTIONS

Questions? Call 866.642.2858 Made with care by Uriel, East Troy, WI 53120 www.urielpharmacy.com